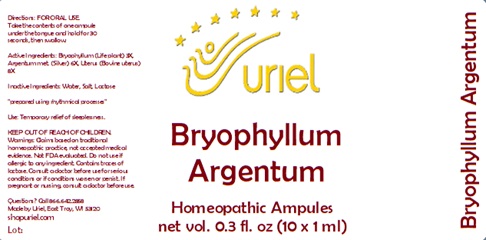 DRUG LABEL: Bryophyllum Argentum
NDC: 48951-2088 | Form: LIQUID
Manufacturer: Uriel Pharmacy Inc.
Category: homeopathic | Type: HUMAN OTC DRUG LABEL
Date: 20240118

ACTIVE INGREDIENTS: KALANCHOE DAIGREMONTIANA LEAF 3 [hp_X]/1 mL; SILVER 6 [hp_X]/1 mL; BOS TAURUS UTERUS 8 [hp_X]/1 mL
INACTIVE INGREDIENTS: SODIUM CHLORIDE; LACTOSE; WATER

Bryophyllum Argentum

INDICATIONS AND USAGE

Directions: FOR ORAL USE.

DOSAGE AND ADMINISTRATION

Take the contents of one ampule under the tongue and hold for 30 seconds, then swallow.

ACTIVE INGREDIENT

Active Ingredients: Bryophyllum (Life plant) 3X, Argentum met. (Silver) 6X, Uterus (Bovine uterus) 8X

Inactive Ingredients: Water, Salt, Lactose

"prepared using rhythmical processes"

PURPOSE

Use: Temporary relief of sleeplessness.

KEEP OUT OF REACH OF CHILDREN.

WARNINGS

Warnings: Claims based on traditional homeopathic practice, not accepted medical evidence. Not FDA evaluated. Do not use if allergic to any ingredient. Contains traces of lactose. Consult a doctor before use for serious conditions or if conditions worsen or persist. If pregnant or nursing, consult a doctor before use.

QUESTIONS

Questions? Call 866.642.2858 Made by Uriel, East Troy, WI 53120 shopuriel.com